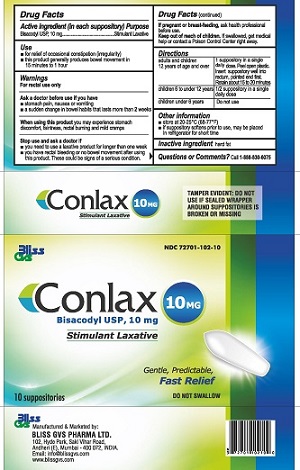 DRUG LABEL: Conlax
NDC: 72701-102 | Form: SUPPOSITORY
Manufacturer: Bliss GVS Pharma Limited
Category: otc | Type: HUMAN OTC DRUG LABEL
Date: 20241221

ACTIVE INGREDIENTS: BISACODYL 10 mg/1 1
INACTIVE INGREDIENTS: FAT, HARD

Conlax (Bisacodyl) Suppositories

Drug Facts

Active ingredient (in each suppository)

Bisacodyl USP, 10 mg

Purpose

Stimulant Laxative

Use

- for relief of occasional constipation (irregularity)
- this product generally produces a bowel movement in 15 minutes to 1 hour

Warnings

For rectal use only

Ask a doctor before use if you have

- stomach pain, nausea or vomiting
- a sudden change in bowel habits that lasts more than 2 weeks

WHEN USING

When using this productyou may experience stomach discomfort, faintness, rectal burning and mild cramps

Stop use and ask a doctor if

- you need to use a laxative product for longer than one week
- you have rectal bleeding or no bowel movement after using this product. These could be signs of a serious condition.

PREGNANCY OR BREAST FEEDING

If pregnant or breast-feeding,ask a health professional before use.

Keep out of reach of children.If swallowed, get medical help or contact a Poison Control Center right away.

Directions

adults and children; 12 years of age and over | 1 suppository in a single daily dose. Peel open plastic. Insert suppository; well into rectum, pointed end first. Retain about 15 to 20 minutes.
children 6 to under 12 years | 1/2 suppository in a single daily dose
children under 6 years | Do not use

Other information

- store at 20-25°C (68-77°F)
- if suppository softens prior to use, may be placed in refrigerator for short time

Inactive ingredienthard fat

Questions or Comments?1-888-830-6075

OTHER SAFETY INFORMATION

TAMPER EVIDENT: DO NOT USE IF SEALED WRAPPER AROUND SUPPOSITORIES IS BROKEN OR MISSING

Manufactured and Marketed by:

BLISS GVS PHARMA LTD.

102, Hyde Park, Saki Vihar Road,

Andheri (E), Mumbai - 400 072, INDIA

Email: info@blissgvs.com

www.blissgvs.com

PACKAGE LABEL

Bliss GVS

NDC 72701-102-10

Conlax 10MG

Bisacodyl USP, 10 mg

Stimulant Laxative

Gentle, Predictable, Fast Relief

10 suppositories

DO NOT SWALLOW